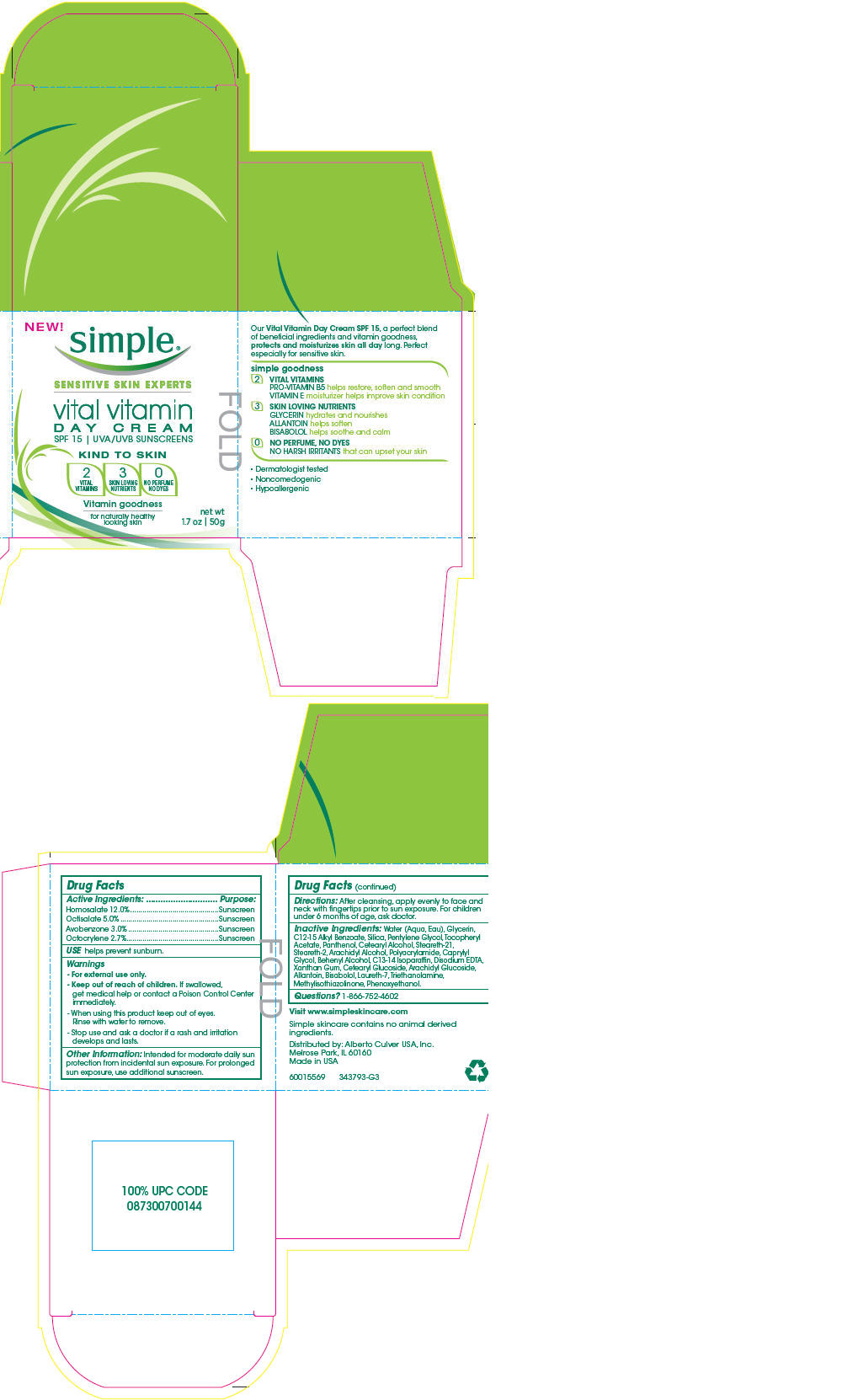 DRUG LABEL: Simple 
NDC: 12488-2000 | Form: EMULSION
Manufacturer: Alberto-Culver USA Inc
Category: otc | Type: HUMAN OTC DRUG LABEL
Date: 20110831

ACTIVE INGREDIENTS: Homosalate 0.12 g/1 g; Octisalate 0.05 g/1 g; Avobenzone 0.03 g/1 g; Octocrylene 0.027 g/1 g
INACTIVE INGREDIENTS: Water; Glycerin; Alkyl (C12-15) Benzoate; Silicon Dioxide; Pentylene Glycol; Panthenol; Cetostearyl Alcohol; Steareth-21; Steareth-2; Arachidyl Alcohol; Caprylyl Glycol; Docosanol; C13-14 Isoparaffin; Edetate Disodium; Xanthan Gum; Cetearyl Glucoside; Arachidyl Glucoside; Allantoin; Levomenol; Laureth-7; Trolamine; Methylisothiazolinone; Phenoxyethanol

simple ®
vital vitamin
DAY CREAM

Drug Facts

ACTIVE INGREDIENT

Active Ingredients: | Purpose:
Homosalate 12.0% | Sunscreen
Octisalate 5.0% | Sunscreen
Avobenzone 3.0% | Sunscreen
Octocrylene 2.7% | Sunscreen

USE

helps prevent sunburn.

Warnings

- For external use only.

- Keep out of reach of children. If swallowed, get medical help or contact a Poison Control Center immediately.

- When using this product keep out of eyes.
  Rinse with water to remove.

- Stop use and ask a doctor if a rash and irritation develops and lasts.

Other Information

Intended for moderate daily sun protection from incidental sun exposure. For prolonged sun exposure, use additional sunscreen.

Directions

After cleansing, apply evenly to face and neck with fingertips prior to sun exposure. For children under 6 months of age, ask doctor.

Inactive Ingredients

Water (Aqua, Eau), Glycerin, C12-15 Alkyl Benzoate, Silica, Pentylene Glycol, Tocopheryl Acetate, Panthenol, Cetearyl Alcohol, Steareth-21, Steareth-2, Arachidyl Alcohol, Polyacrylamide, Caprylyl Glycol, Behenyl Alcohol, C13-14 Isoparaffin, Disodium EDTA, Xanthan Gum, Cetearyl Glucoside, Arachidyl Glucoside, Allantoin, Bisabolol, Laureth-7, Triethanolamine, Methylisothiazolinone, Phenoxyethanol.

Questions?

1-866-752-4602

Distributed by: Alberto Culver USA, Inc.
Melrose Park, IL 60160

PRINCIPAL DISPLAY PANEL - 50g Jar Carton

NEW!

simple ®

SENSITIVE SKIN EXPERTS

vital vitamin
DAY CREAM
SPF 15 | UVA/UVB SUNSCREENS

KIND TO SKIN

2
VITAL
VITAMINS

3
SKIN LOVING
NUTRIENTS

0
NO PERFUME
NO DYES

Vitamin goodness
for naturally healthy
looking skin

net wt
1.7 oz | 50g